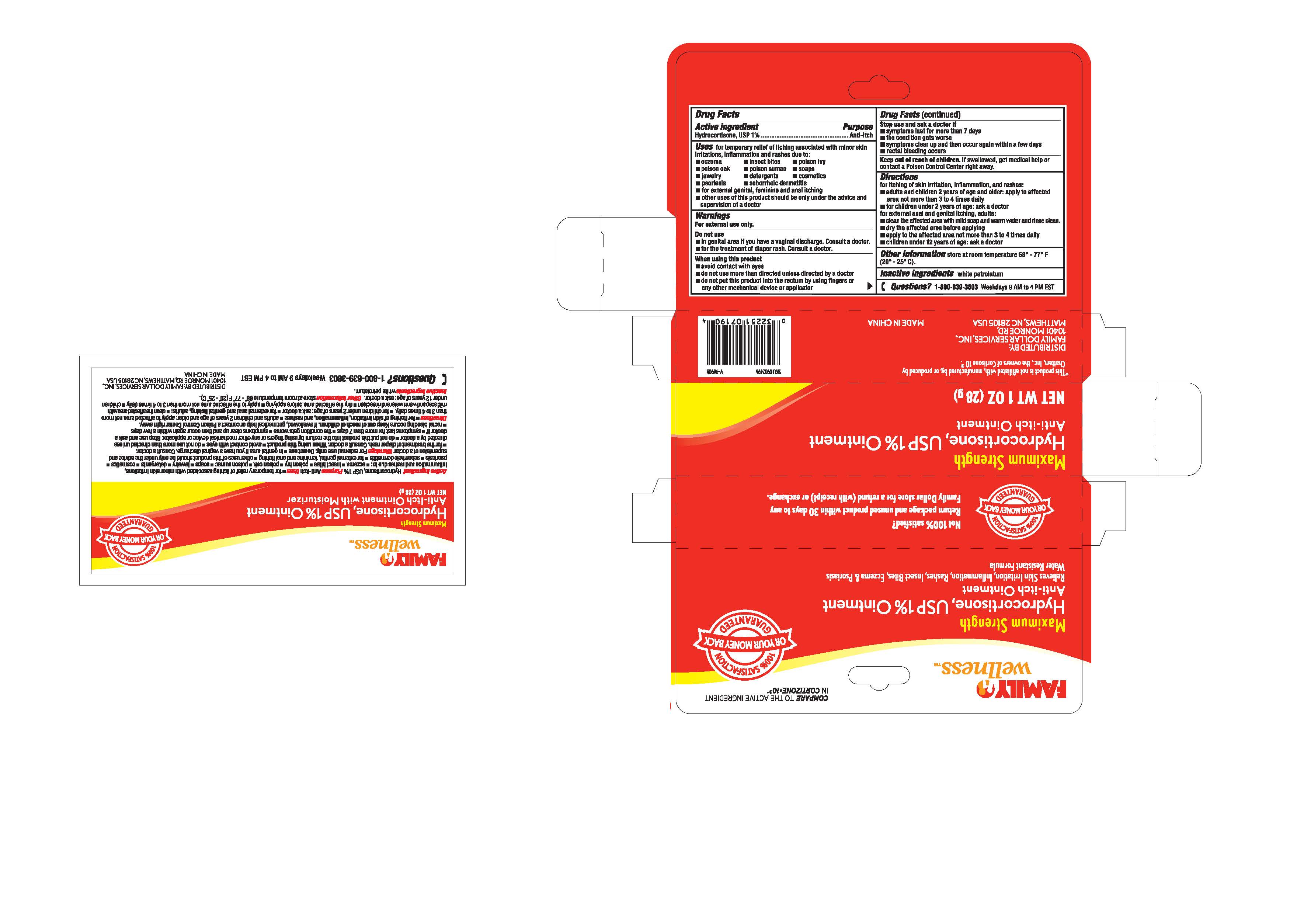 DRUG LABEL: Family Wellness

NDC: 55621-008 | Form: CREAM
Manufacturer: Zhejiang Jingwei Pharmaceutical Co., Ltd.
Category: otc | Type: HUMAN OTC DRUG LABEL
Date: 20231024

ACTIVE INGREDIENTS: HYDROCORTISONE 1 g/100 g
INACTIVE INGREDIENTS: PETROLATUM

Drug Facts

Inactive Ingredients white petrolatum

Active Ingredient

Hydrocortisone, USP 1%

Purpose

Anti-itch

INDICATIONS AND USAGE

Uses - for temporary relief of itching associated with minor skin irritations, inflammation and rashes due to:

-eczema -insect bites -poison ivy

-poison oak -poison sumac -soaps

-jewelry -detergents -cosmetics

-psoriasis -seborrheic dermatitis

-for external genital, feminine and anal itching

-other uses of this product should be only under the advice and

supervision of a doctor

Keep out of reach of children. If swallowed, get medical help or contact a

Poison Control Center right away.

Warnings

For external use only.

Do not use

-in genital area if you have a vaginal discharge. Consult a doctor.

-for the treatment of diaper rash, Consult a doctor.

When using this product

-avoid contact with eyes

-do not use more than directed unless directed by a doctor

-do not put this product into the rectum by using fingers or any other mechanical device or applicator

Stop use and ask a doctor if

-symptoms last for more than 7 days

-the conditions get worse

-symptoms clear up and then occur again within a few days

-rectal bleeding occurs

Directions

for itching of skin irritation, inflammation and rashes:

-adults and children 2 years of age and older: apply to affected area not more than 3 or 4 times daily

-for children under 2 years of age: ask a doctor

for external anal and genital itching:

adults:

-clean the affected area with mild soap and warm water and rinse clean.

-dry the affected area before applying

-apply to the affected area not more than 3 to 4 times daily

-children under 12 years of age: ask a doctor

Other Information store at room temperature 68-77 F (20-25 C)

QUESTIONS

Questions? 1-800-639-3803 Weekdays 9AM to 4 PM EST